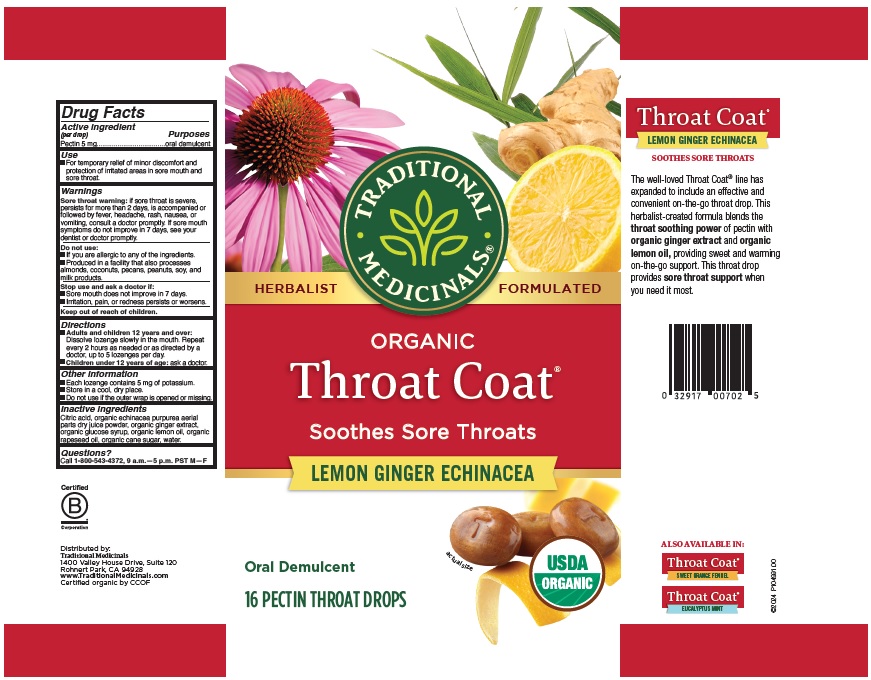 DRUG LABEL: Throat Coat
NDC: 78732-100 | Form: LOZENGE
Manufacturer: Traditional Medicinals, Inc.
Category: otc | Type: HUMAN OTC DRUG LABEL
Date: 20251121

ACTIVE INGREDIENTS: PECTIN 5 mg/4.2 g
INACTIVE INGREDIENTS: CITRIC ACID MONOHYDRATE; CANOLA OIL; CORN SYRUP; WATER; RAW SUGAR; ECHINACEA, UNSPECIFIED; LEMON OIL; GINGER

Organic Throat Coat - Lemon Ginger Echinacea

Active ingredient

Active ingredient (per drop) Pectin 5 mg

Purpose

Purpose oral demulcent

Uses

For temporary relief of minor discomfort and protection of irritated areas in sore mouth and sore throat.

Warnings

Sore throat warning: if sore throat is severe, persists for more than 2 days, is accompanied or followed by fever, headache, rash, nausea, or vomiting, consult a doctor promptly. If sore mouth symptoms do not improve in 7 days see your dentist or doctor promptly.

Do not use

- If you are allergic to any of the ingredients.
- Manufactured in a facility that also handles coconut oil

Stop use and ask a doctor if:

- Sore mouth does not improve in 7 days
- irritation, pain, or redness persistst or worsesns.

Keep out of reach of children

Directions

- Adults and children 12 years and over: Dissolve lozenge slowly in the mouth. Repeat every 2 hours as needed or as directed by a doctor, up to 5 lozenges per day
- Children under 12 years of age: ask a doctor.

Other information

- Each lozenge contains 20 mg of potassium.
- Store in a cool, dry place.
- Do not use if the outer wrap is opened or missing.

Inactive ingredients

Citric acid, organic echinacea extract, organic ginger extract, organic glucose syrup, organic lemon oil, organic rapeseed oil, organic raw cane sugar, water.

Questions

call 1-800-543-4372, 9 a.m. - 5 p.m. PST M-F

TRADITIONAL MEDICINALS®

ORGANIC Throat Coat®

Soothes Sore Throats

LEMON GINGER ECHINACEA

Oral Demulcent

16 PECTIN THROAT DROPS

Distributed by:

Traditional Medicinals

1400 Valley House Dr, Suite 120

Rohnert Park, CA 94928

www.TraditionalMedicinals.com

Certified organic by CCOF